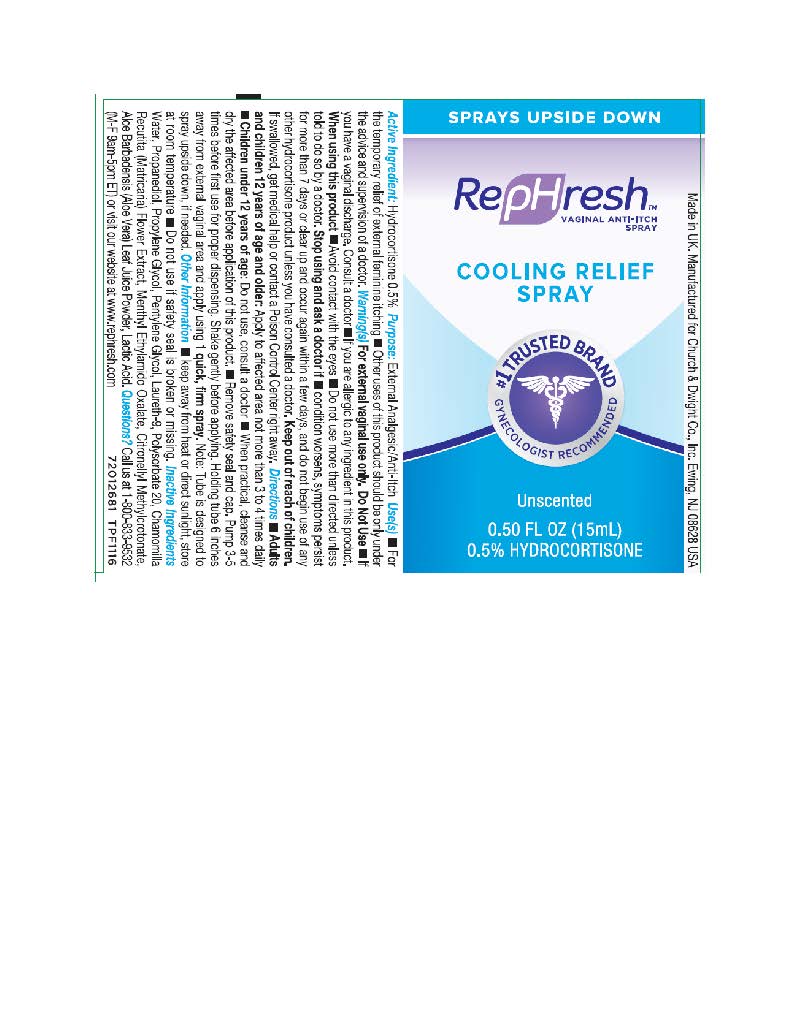 DRUG LABEL: Rephresh Cooling
NDC: 70233-774 | Form: SPRAY
Manufacturer: Fleet Laboratories LTD
Category: otc | Type: HUMAN OTC DRUG LABEL
Date: 20180612

ACTIVE INGREDIENTS: HYDROCORTISONE 500 g/1 g
INACTIVE INGREDIENTS: CITRONELLYL METHYLCROTONATE; POLYSORBATE 20; POLIDOCANOL; PROPANEDIOL; ALOE VERA LEAF; MATRICARIA CHAMOMILLA; MENTHYL ETHYLENE GLYCOL CARBONATE, (-)-; LACTIC ACID; PENTYLENE GLYCOL; MATRICARIA RECUTITA FLOWERING TOP; WATER; PROPYLENE GLYCOL

RepHresh Spray

ACTIVE INGREDIENT

Hydrocortisone 0.5%

PURPOSE

External Analgesic/Anti-Itch

USE

For the temporary relief of external feminine itching

Other uses of this product should be only under the advice and supervision of a doctor

WARNINGS

Warning(s) For external vaginal use only

ASK DOCTOR/PHARMACIST

Consult a doctor if you are allergic to any ingredient in this product

WHEN USING

Avoid contact with eyes

Do not use if you have vaginal discharge

Do not use more than directed unless told to do so by a doctor

Stop use and ask a doctor if condition worsens, symptoms persists for more than 7 days or clear up and occur again within a few days, and do not begin use of any other hydrocortisone product unless you have consulted a doctor

Keep out of reach of children

If swallowed, get medical help or contact a Poison Control Center right away

Directions

Adults and children under 12 years of age and older: Apply to affected area not more than 3 to 4 times daily

Children under 12 years of age: Do not use, consult a doctor

When practical, cleanse and dry the affected area before application of this product

Remove safety seal and cap

DOSAGE AND ADMINISTRATION

Pump 3-5 times before first use for proper dispensing

Shake gently before applying

Holding tube 6 inches away from vaginal are and apply using 1 quick, firm spray.

Note: Tube is designed to spray upside down, if needed

OTHER SAFETY INFORMATION

Keep away from hear or direct sunlight, store at room temperature

Do not use if safety seal is broken or missing

INACTIVE INGREDIENT

Water, Propanediol, Propylene Glycol, Pentylene Glycol, Laureth-9, Polysorbate 20, Chamomilla Recutita (Matricaria) Flower Extract, Menthyl Ethylamido Oxalate, Citronellyl Methylcrotonate, Aloe Barbadensis (Aloe Vera) Leaf Juice Powder, Lactic Acid

QUESTIONS

Questions? Call us at 800 833 9532 Monday through Friday 9 to 5 pm ET or visit our website at www rephresh com

PACKAGE LABEL

RepHresh™ Vaginal Anti-Itch Spray

Cooling Relief Spray

#1 Trusted Brand

Gynecologist Recommended

Unscented

0.50 FL OZ (15mL)

0.5% Hydrocortisone